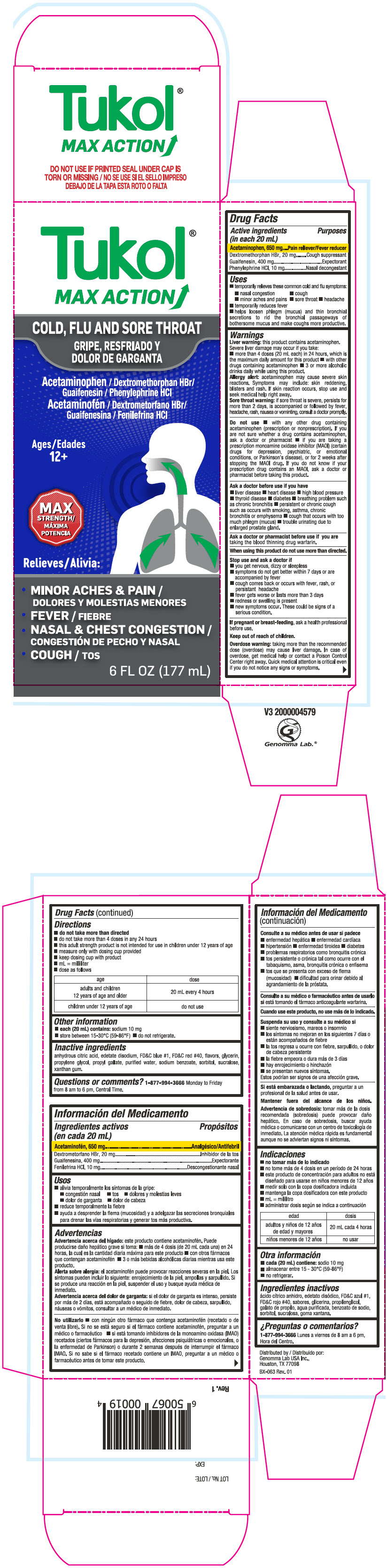 DRUG LABEL: Tukol Max Action Cold, Flu and Sore Throat
NDC: 50066-313 | Form: SYRUP
Manufacturer: Genomma Lab USA
Category: otc | Type: HUMAN OTC DRUG LABEL
Date: 20240614

ACTIVE INGREDIENTS: Acetaminophen 32.5 mg/1 mL; Dextromethorphan Hydrobromide 1 mg/1 mL; Guaifenesin 20 mg/1 mL; Phenylephrine Hydrochloride 0.5 mg/1 mL
INACTIVE INGREDIENTS: Water; Glycerin; Propylene Glycol; Sorbitol; Sodium benzoate; Sucralose

Tukol® Max Action Cold, Flu and Sore Throat

Drug Facts

ACTIVE INGREDIENT

PURPOSE

Active ingredients (in each 20 mL) | Purposes
Acetaminophen 650mg | Pain reliever/fever reducer
Dextromethorphan HBr 20 mg | Cough suppressant
Guaifenesin 400 mg | Expectorant
Phenylephrine HCl 10 mg | Nasal decongestant

Uses

- temporarily relieves these common cold and flu symptoms:
  - nasal congestion
  - cough
  - minor aches and pains
  - sore throat
  - headache
  - temporarily reduces fever
  - helps loosen phlegm (mucus) and thin bronchial secretions to rid the bronchial passageways of bothersome mucus and make coughs more productive

Warnings

Liver warning

This product contains acetaminophen.

Severe liver damage may occur if you take:

- more than 4 doses (20 mL each) in 24 hours, which is the maximum daily amount for this product.
- with other drugs containing acetaminophen
- 3 or more alcoholic drinks daily while using this product.

Allergy alert

Acetaminophen may cause severe skin reactions. Symptoms may include: skin reddening, blisters and rash.

If skin reaction occurs, stop use and seek medical help right away.

Sore throat warning

if sore throat is severe, persists for more than 2 days, is accompanied or followed by fever, headache, rash, nausea or vominting, consult a doctor promptly.

Do not use

- with any other drug containing acetaminophen (prescription or nonprescription). If you are not sure whether a drug contains acetaminophen, ask a doctor or pharmacist
- if you are taking a prescription monoamine oxidase inhibitor (MAOI) (certain drugs for depression, psychiatric, or emotional conditions, or Parkinson's disease), or for 2 weeks after stopping the MAOI drug. If you do not know if your prescription drug contains an MAOI, ask a doctor or pharmacist before taking this product.

Ask a doctor before use if you have

- liver disease
- heart disease
- high blood pressure
- thyroid disease
- diabetes
- a breathing problem such as chronic bronchitis
- persistent or chronic cough such as occurs with smoking, asthma chronic, bronchitis or emphysema
- cough that occurs with too much phlegm (mucus)
- trouble urinating due to enlarged prostate gland

Ask a doctor or pharmacist before use if you are taking the blood thinning drug warfarin

When using this product do not use more than directed

Stop use and ask a doctor if

- you get nervous, dizzy or sleepless
- pain, nasal congestion or cough gets worse or lasts more than 7 days
- cough comes back or occuurs with fever, rash, or headache that lasts
- fever gets worse or lasts more than 3 days
- redness or swelling is present
- new symptoms occur.

These could be signs of a serious condition.

PREGNANCY OR BREAST FEEDING

If pregnant or breast-feeding, ask a health professional before use.

Keep out of reach of children.

Taking more than the recommended dose (overdose) may cause liver damage. In case of overdose, get medical help or contact a Poison Control Center right away. Quick medical attention is critical even if you do not notice any signs or symptoms.

Directions

- do not take more than directed
- Do not take more than 4 doses in 24 hours.
- This adult strength product is not intended for use in children under 12 years of age
- Dose as follows or as directed by a doctor
- Use dose cup provided

age | dose
adults and children 12 years and older | 20 mL every 4 hours
children under 12 years of age | do not use

Other information

- each 20 mL contains: sodium 10 mg
- store between 15-30°C (59-86°F), do not refrigerate

Inactive ingredients

Anhydrous citric acid, edetate disodium, FD&C Blue # 1, FD&C Red # 40, flavors, glycerin, propylene glycol, propyl gallate, purified water, sodium benzoate, sorbitol, sucralose, xanthan gum

Questions or comments?

1-877-994-3666

Monday to Friday from 8 AM to 6 PM, Central time.

Distributed by:
Genomma Lab USA Inc.,
Houston, TX 77027

PRINCIPAL DISPLAY PANEL - 177 mL Bottle Carton

Tukol®
MAX ACTION

COLD, FLU AND SORE THROAT

Acetaminophen / Dextromethorphan HBr/
Guaifenesin / Phenylephrine HCl

Ages
12+

MAX
STRENGTH

Relieves:

- MINOR ACHES & PAIN
- FEVER
- NASAL & CHEST CONGESTION
- COUGH

6 FL OZ (177 mL)